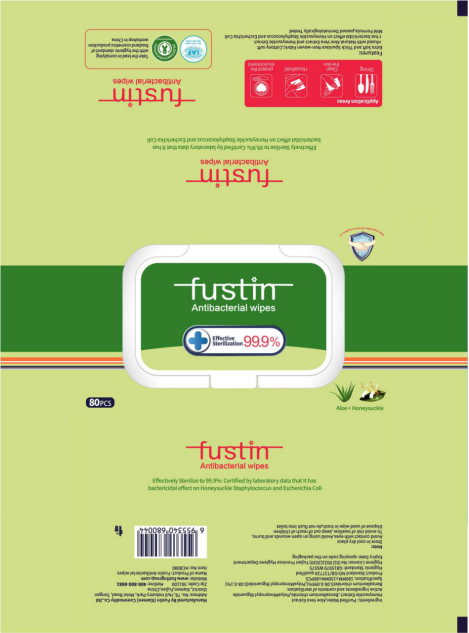 DRUG LABEL: FUSTIN ANTIBACTERIAL WIPES
NDC: 42129-008 | Form: CLOTH
Manufacturer: Fustin (Xiamen) Commodity Co., Ltd.
Category: otc | Type: HUMAN OTC DRUG LABEL
Date: 20200427

ACTIVE INGREDIENTS: POLYAMINOPROPYL BIGUANIDE 0.342 mg/80 1; BENZALKONIUM CHLORIDE 0.3325 mg/80 1
INACTIVE INGREDIENTS: ALOE VERA LEAF; WATER

DOSAGE AND ADMINISTRATION

Keep away from flame or high heat.

INACTIVE INGREDIENT

Purified Water

Aloe Vera Extract

Honeysuckle Extract

INDICATIONS AND USAGE

Open the upper cover, open the unsealing glue, pull out the wet wipes.

ACTIVE INGREDIENT

Benzalkonium Chloride

Polyaminopropyl Biguanide

keep out of children

PURPOSE

Disinfection
Sterilization
No Rinseing

WARNINGS

Please place it out of reach of infants to avoid eating by mistake.his product is insoluble in water, please throw it into the garbage can after use.